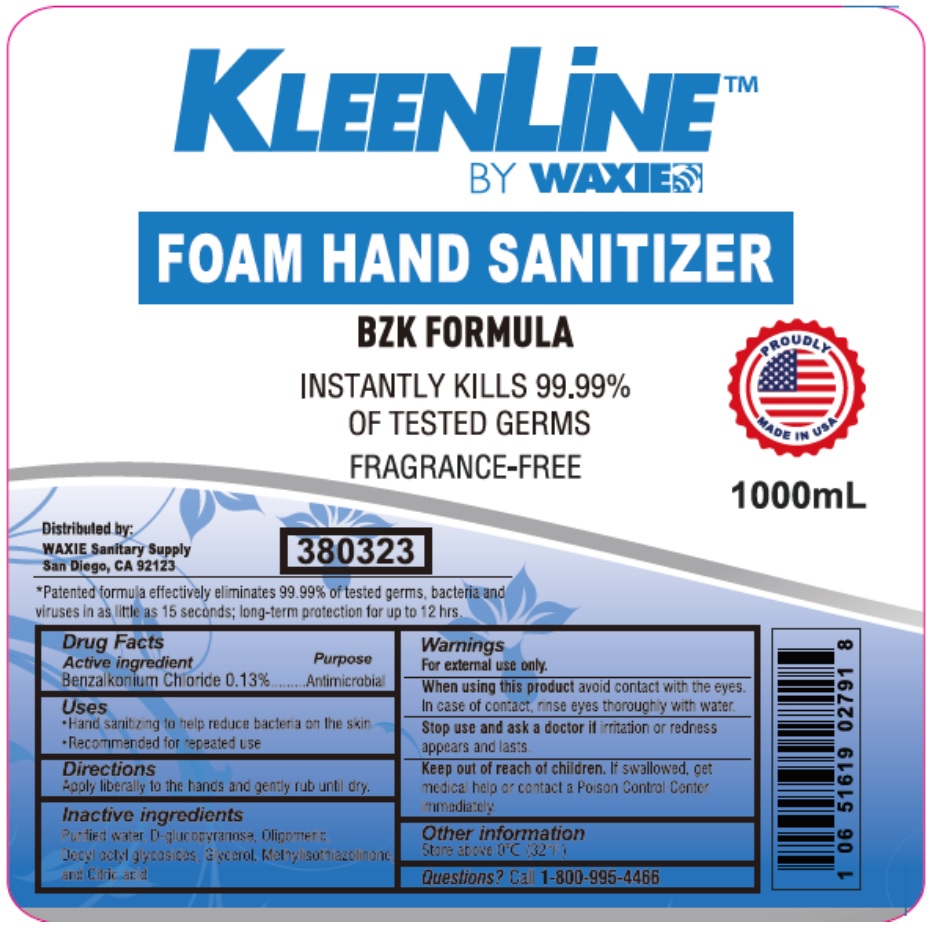 DRUG LABEL: KLEENLINE FOAM HAND SANITIZER
NDC: 78168-618 | Form: LIQUID
Manufacturer: Teh Tung Corporation
Category: otc | Type: HUMAN OTC DRUG LABEL
Date: 20210301

ACTIVE INGREDIENTS: BENZALKONIUM CHLORIDE 0.13 g/100 mL
INACTIVE INGREDIENTS: WATER; CAPRYLYL/CAPRYL OLIGOGLUCOSIDE; GLYCERIN; METHYLISOTHIAZOLINONE; CITRIC ACID MONOHYDRATE

KLEENLiNE™ BY WAXIE FOAM HAND SANITIZER

Active ingredient

Benzalkonium Chloride 0.13%

Purpose

Antimicrobial

Uses

• Hand sanitizing to help reduce bacteria on the skin

• Recommended for repeated use

Directions

Apply liberally to the hands and gently rub until dry.

Inactive ingredients

Purified water, D-glucopyranose, Oligomeric, Decyl octyl glycosides, Glycerol, Methylisothiazolinone and Citric acid

Warnings

For external use only.

When using this product avoid contact with the eyes. In case of contact, rinse eyes thoroughly with water.

Stop use and ask a doctor if irritation or redness appears and lasts.

Keep out of reach of children. If swallowed, get medical help or contact a Poison Control Center immediately.

Other information

Store above 0°C (32°F)

Questions?

Call 1-800-995-4466

BZK FORMULA

INSTANTLY KILLS 99.99% OF TESTED GERMS

FRAGRANCE-FREE

PROUDLY MADE IN USA

Distributed by:

WAXIE Sanitary Supply

San Diego, CA 92123

*Patented formula effectively eliminates 99.99% of tested germs, bacteria and viruses in as little as 15 seconds; long-term protection for up to 12 hrs.